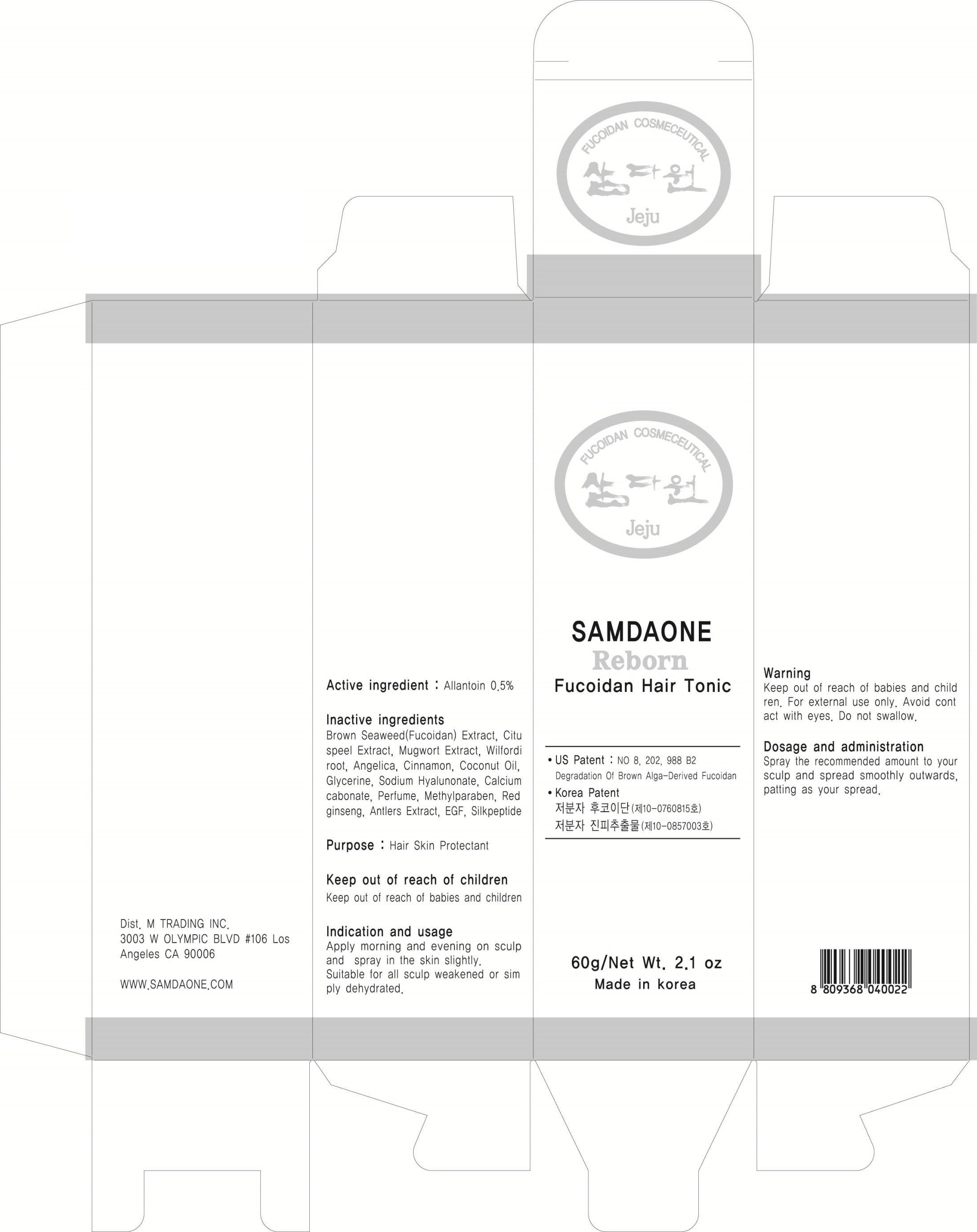 DRUG LABEL: FUCOIDAN HAIR TONIC
NDC: 58986-030 | Form: SPRAY
Manufacturer: SAMDAONE
Category: otc | Type: HUMAN OTC DRUG LABEL
Date: 20130822

ACTIVE INGREDIENTS: Allantoin 0.3 g/60 g
INACTIVE INGREDIENTS: Glycerin; Methylparaben

ACTIVE INGREDIENT

Active ingredient: Allantoin 0.5%

INACTIVE INGREDIENT

Inactive ingredients:
Brown Seaweed(Fucoidan) Extract, Red ginseng, Amtlers Extract, Cituspeel Extract, Mugwort Extract, Wilfordi root, Angelica, Cinnamon, Coconut Oil, Glycerin, Sodium Hyalunonate, Calciam cabonate, Perfume, Methylparaben, EGF, Silkpeptide

PURPOSE

Purpose: Hair Skin Protectant

WARNINGS

Warning:
Keep out of reach of babies and children.
For external use only.
Avoid contact with eyes.
Do not swallow.

KEEP OUT OF REACH OF CHILDREN

Keep out of reach of babies and children.

INDICATIONS AND USAGE

Indication and usage:
Apply morning and evening on sculp and spray in the skin slightly.
Suitable for all sculp weakened or simply dehydrated.

DOSAGE AND ADMINISTRATION

Spray the recommended amount to your sculp and spread smoothly outwards, patting as your spread.